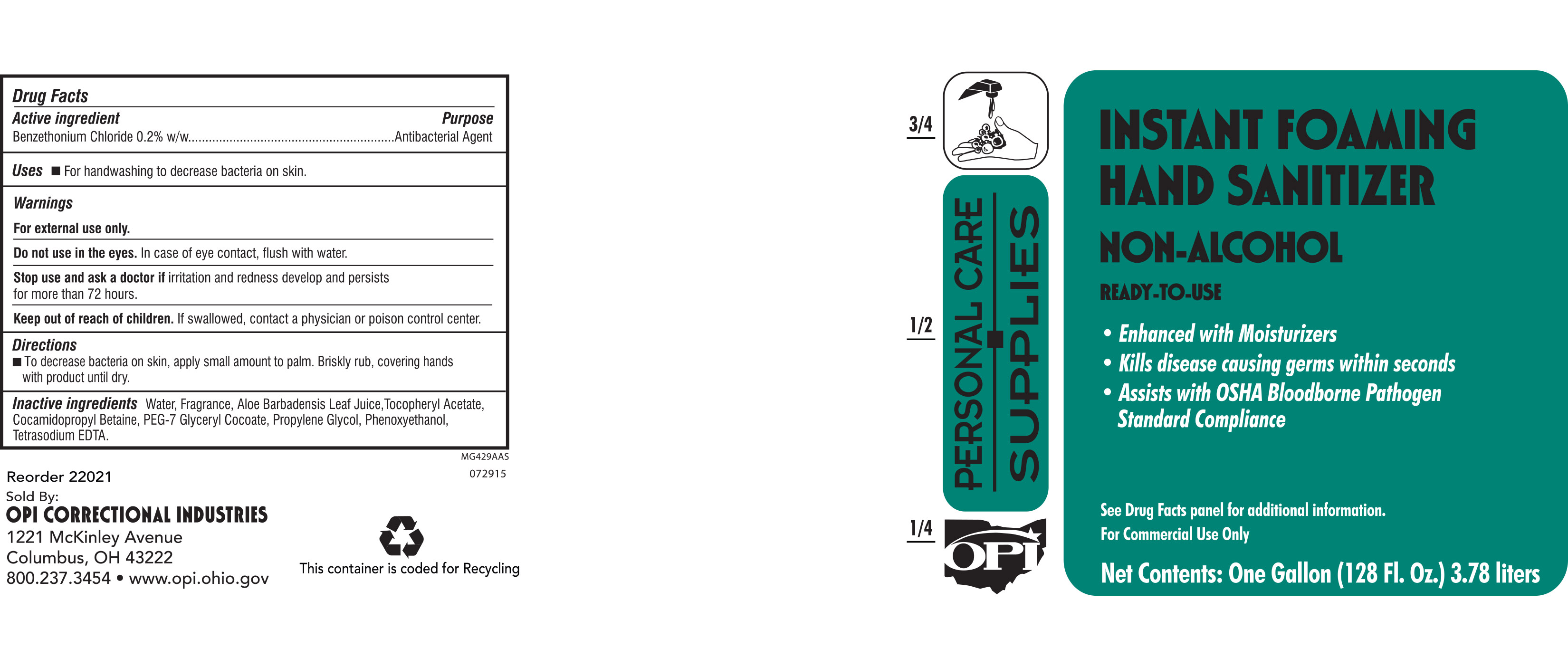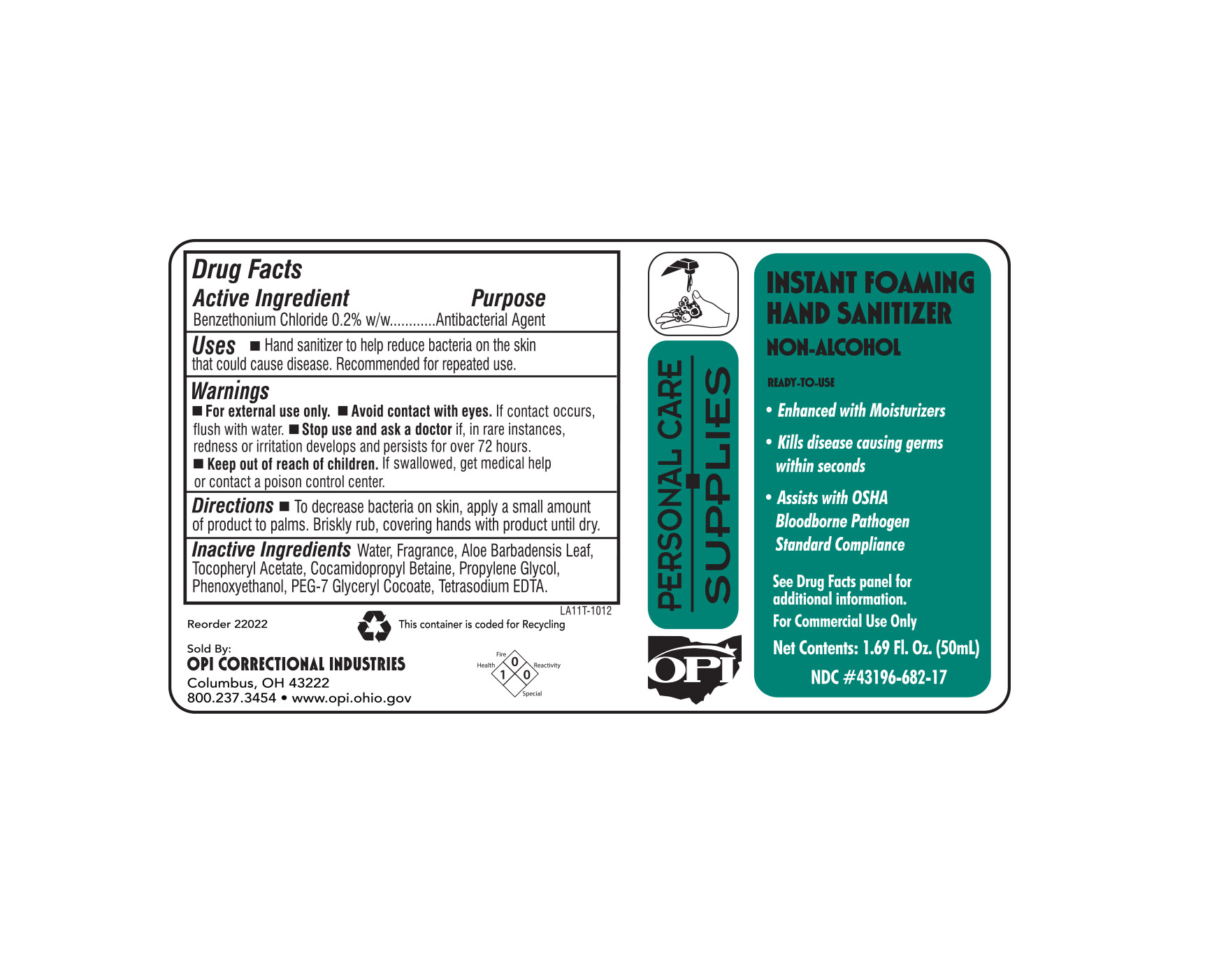 DRUG LABEL: Foaming Instant Hand Sanitizer with Aloe and Vitamin E
NDC: 43196-207 | Form: SOLUTION
Manufacturer: OPI Correctional Industries
Category: otc | Type: HUMAN OTC DRUG LABEL
Date: 20160705

ACTIVE INGREDIENTS: BENZETHONIUM CHLORIDE 7.56 g/100 mL
INACTIVE INGREDIENTS: WATER; EDETATE SODIUM; COCAMIDOPROPYL BETAINE; PEG-7 GLYCERYL COCOATE; PROPYLENE GLYCOL; PHENOXYETHANOL; ALOE VERA LEAF; .ALPHA.-TOCOPHEROL ACETATE, DL-

Foaming Instant Hand Sanitizer with Aloe and Vitamin E

ACTIVE INGREDIENT

Benzethonium Chloride 0.2% w/w.....Antibacterial Agent

INACTIVE INGREDIENT

Water, Fragrance, Aloe Barbadensis Leaf, Tocopheryl Acetate, Cocamidopropyl Betaine, Propylene Glycol, Phenoxyethanol, PEG-7 Glyceryl Cocoate, Tetrasodium EDTA.

PURPOSE

Hand sanitizer to help reduce bacteria on the skin that could cause disease. Recommended for repeated use.

WARNINGS

For external use only.

Avoid contact with eyes. If contact occurs, flush with water.

Stop use if, in rare instances, redness or irritation develop. If condition persists for more than 72 hours, consult a physician.

Keep out of reach of children. If swallowed, contact a physician or poison control center.

DOSAGE AND ADMINISTRATION

To decrease bacteria on skin, apply small amount to palm. Briskly rub, covering hands with product until dry.

INDICATIONS AND USAGE

Hand sanitizer to help reduce bacteria on the skin that could cause disease. Recommended for repeated use.

Avoid contact with eyes. If contact occurs, flush with water.

Stop use if, in rare instances, redness or irritation develop. If condition persists for more than 72 hours, consult a physician.

Keep out of reach of children. If swallowed, contact a physician or poison control center.

Keep out of reach of children. If swallowed, contact a physician or poison control center.